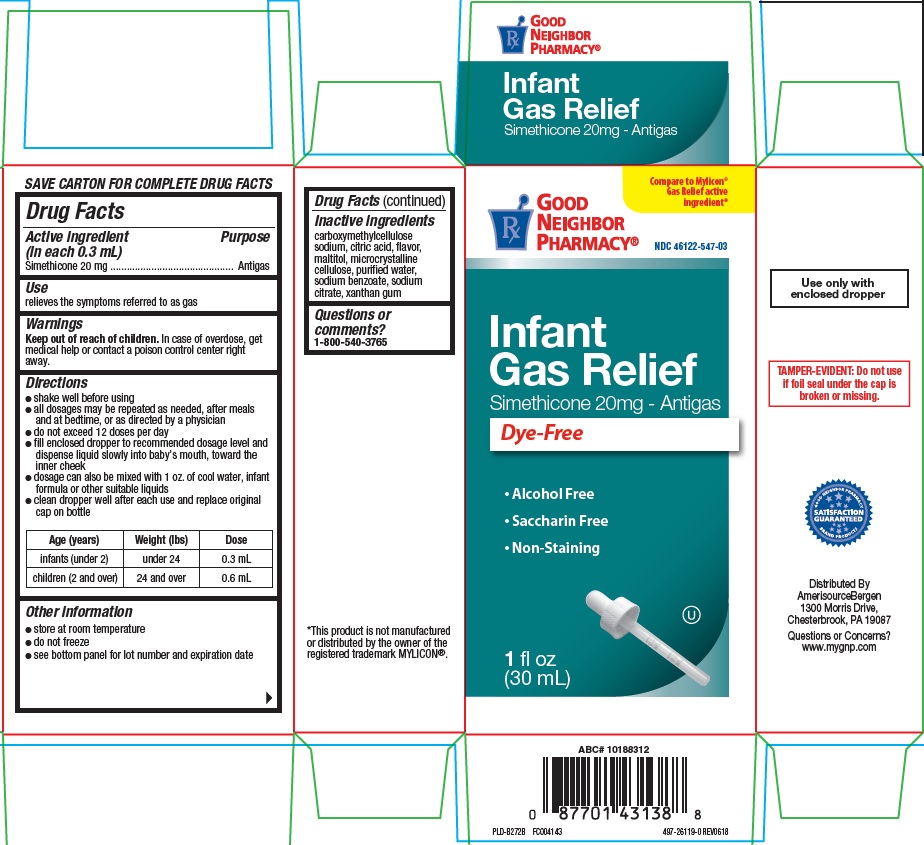 DRUG LABEL: INFANT GAS RELIEF
NDC: 46122-547 | Form: SUSPENSION/ DROPS
Manufacturer: AMERISOURCEBERGEN DRUG CORPORATION
Category: otc | Type: HUMAN OTC DRUG LABEL
Date: 20230718

ACTIVE INGREDIENTS: DIMETHICONE 20 mg/0.3 mL
INACTIVE INGREDIENTS: CARBOXYMETHYLCELLULOSE SODIUM; ANHYDROUS CITRIC ACID; MALTITOL; CELLULOSE, MICROCRYSTALLINE; WATER; SODIUM BENZOATE; SODIUM CITRATE; XANTHAN GUM

GNP infant drops

Active ingredient (in each 0.3 mL)

Simethicone 20 mg

Purpose

Antigas

Use

relieves the symptoms referred to as gas

Warnings

Keep out of reach of children. In case of overdose, get medical help or contact a poison control center right away.

Directions

- shake well before using
- all dosages may be repeated as needed, after meals and at bedtime, or as directed by a physician
- do not exceed 12 doses per day
- fill enclosed dropper to recommended dosage level and dispense liquid slowly into baby’s mouth, toward inner cheek
- dosage can also be mixed with 1 oz. of cool water, infan formula or other suitable liquids
- clean dropper well after each use and replace original cap on bottle

Age (years) | Weight (lbs) | Dose
infants (under 2) | under 24 | 0.3 mL
children (over 2) | 24 and over | 0.6 mL

Other information

- store at room temperature
- do not freeze
- see bottom panel for lot number and expiration date

Inactive ingredients

carboxymethylcellulose sodium, citric acid, flavor, maltitol, microcrystalline cellulose, purified water, sodium benzoate, sodium citrate, xanthan gum.

Questions or comments?

1-800-540-3765